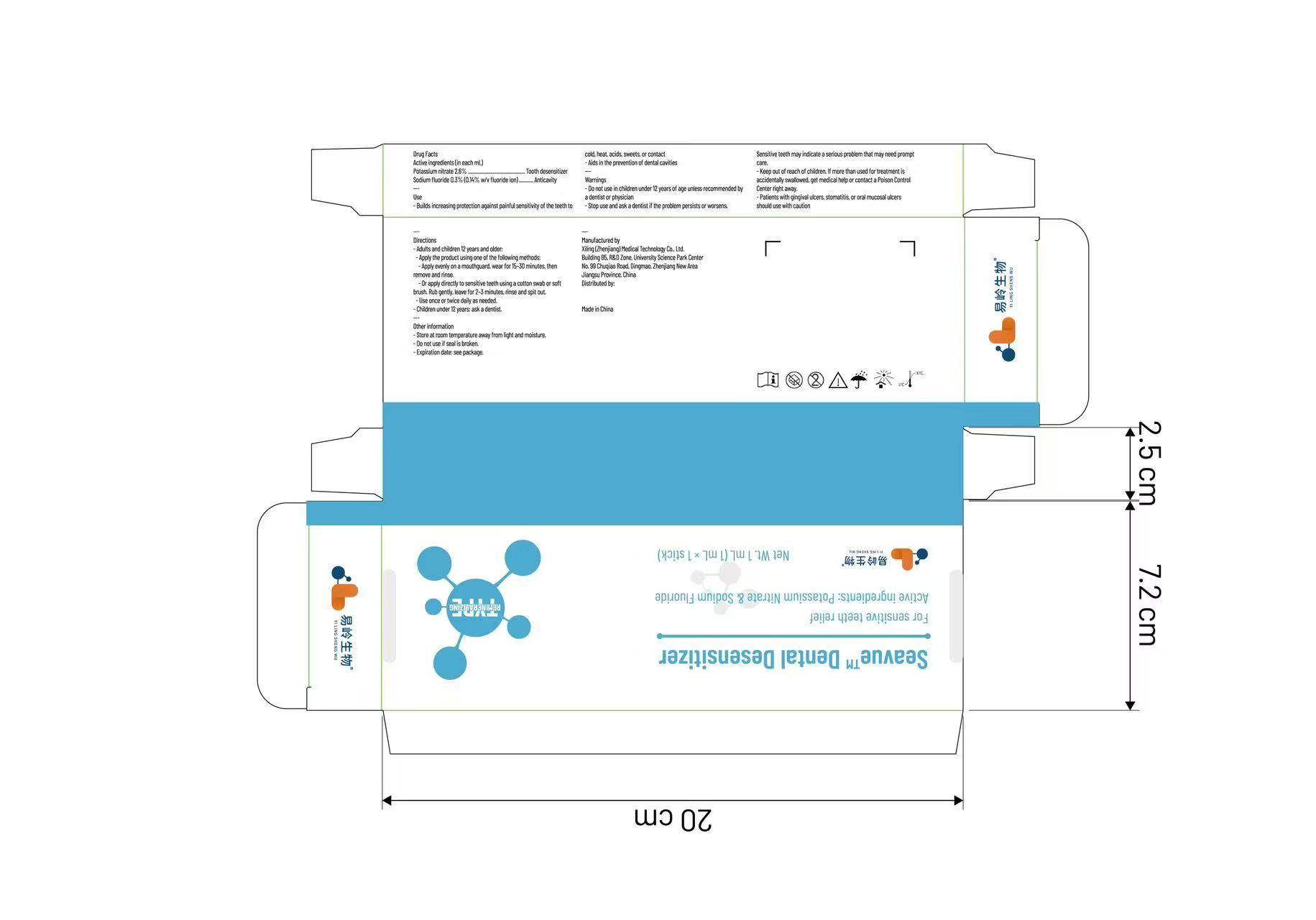 DRUG LABEL: Seavue Dental Desensitizer
NDC: 87118-003 | Form: GEL, DENTIFRICE
Manufacturer: Xiling (Zhenjiang) Medical Technology Co., Ltd.
Category: otc | Type: HUMAN OTC DRUG LABEL
Date: 20250920

ACTIVE INGREDIENTS: SODIUM FLUORIDE 1.36 mg/1 g; POTASSIUM NITRATE 26 mg/1 g

ACTIVE INGREDIENT

Potassium nitrate, Sodium fluoride

Stop use and ask a doctor if irritation, swelling, or allergic reaction occurs.

Do not use in children under 12 years of age unless recommended by a dentist or physician

Keep out of reach of children. If more than used for treatment is accidentally swallowed, get medical help or contact a Poison Control Center right away.

PURPOSE

Oral antiseptic

WHEN USING

Use once or twice daily as needed.

Dosage:

Potassium nitrate 2.6% ................................................ Tooth desensitizer
Sodium fluoride 0.3% (0.14% w/v fluoride ion) ............ Anticavity

Use:

Builds increasing protection against painful sensitivity of the teeth to cold, heat, acids, sweets, or contact
Aids in the prevention of dental cavities

Do not use in children under 12 years of age unless recommended by a dentist or physician
Stop use and ask a dentist if the problem persists or worsens. Sensitive teeth may indicate a serious problem that may need prompt care.
Keep out of reach of children. If more than used for treatment is accidentally swallowed, get medical help or contact a Poison Control Center right away.
Patients with gingival ulcers, stomatitis, or oral mucosal ulcers should use with caution.

INACTIVE INGREDIENT

None

INDICATIONS AND USAGE

Adults and children 12 years and older:

Apply the product using one of the following methods:

Apply evenly on a mouthguard, wear for 15–30 minutes, then remove and rinse.
Or apply directly to sensitive teeth using a cotton swab or soft brush. Rub gently, leave for 2–3 minutes, rinse and spit out.

Use once or twice daily as needed.

Children under 12 years: ask a dentist.